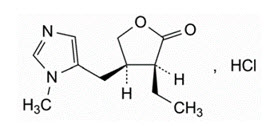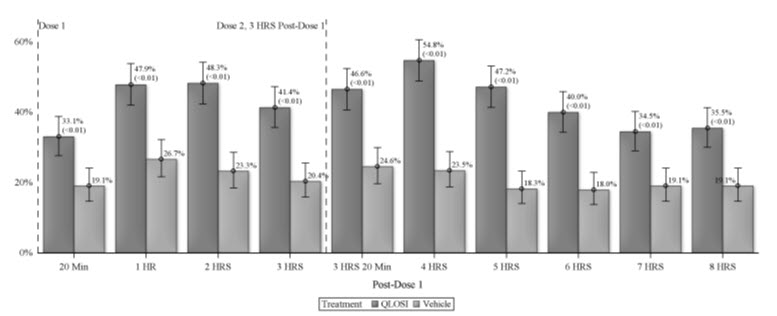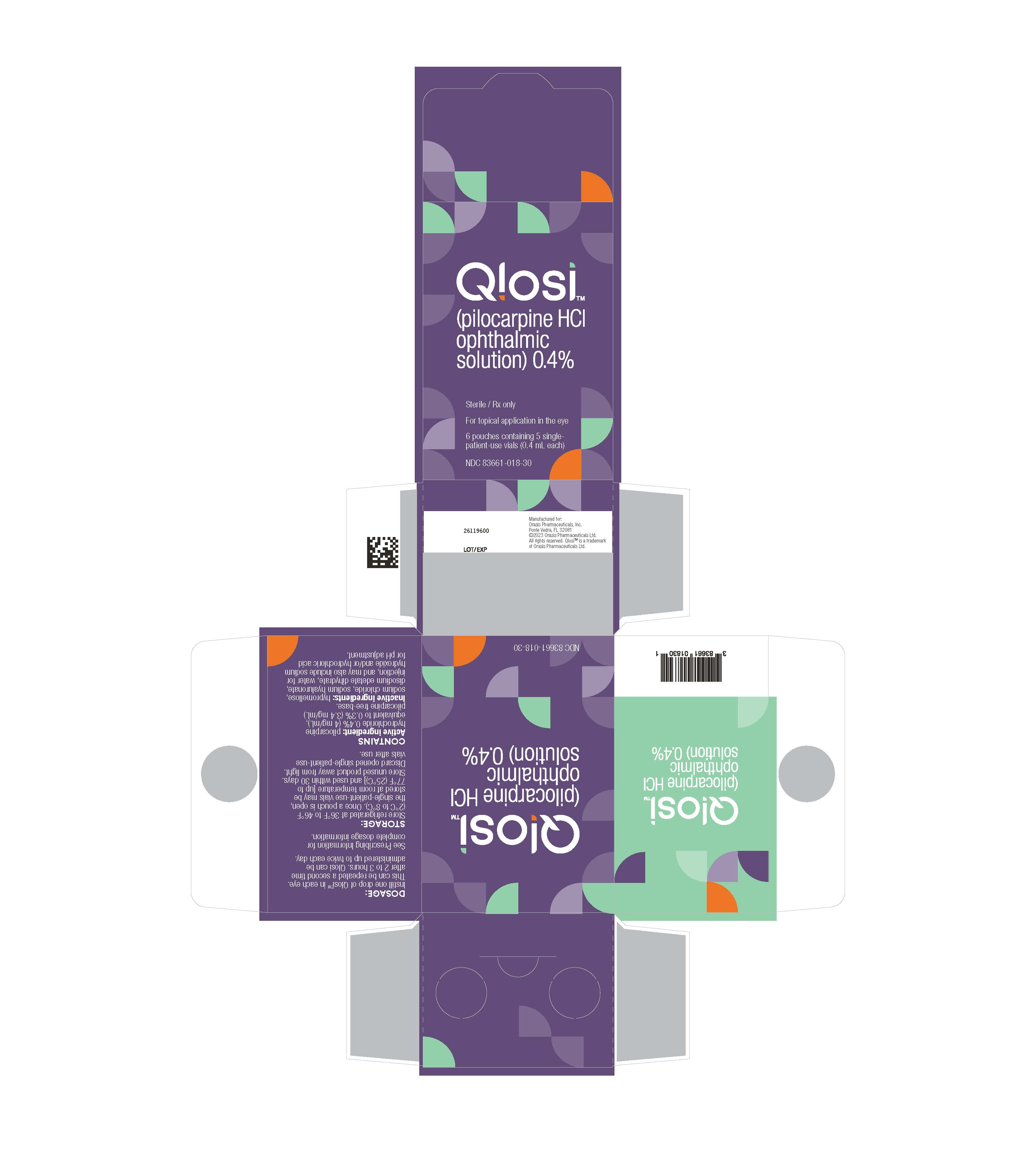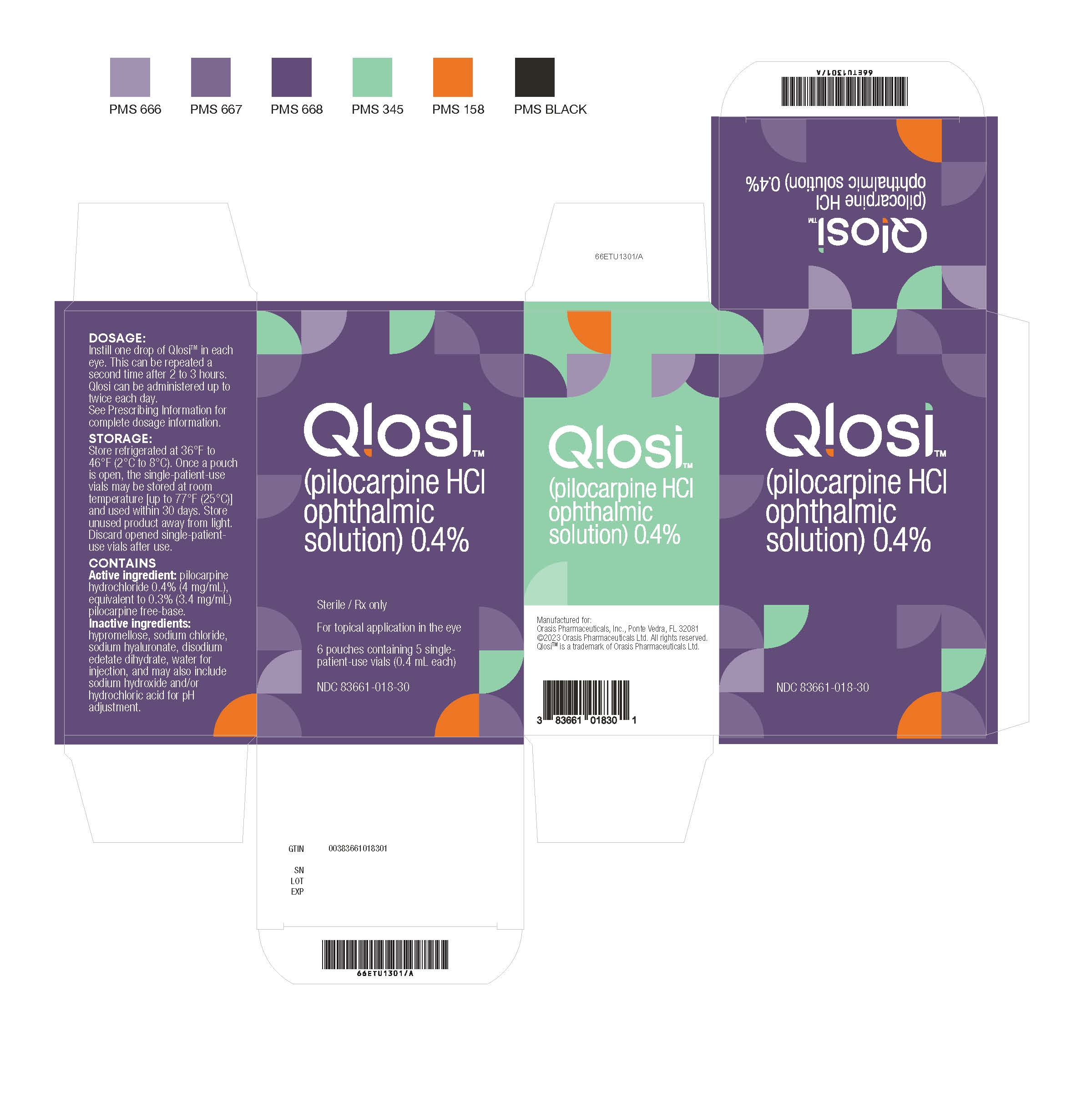 DRUG LABEL: Qlosi
NDC: 83661-018 | Form: SOLUTION
Manufacturer: Orasis Pharmaceuticals, Inc.
Category: prescription | Type: HUMAN PRESCRIPTION DRUG LABEL
Date: 20250530

ACTIVE INGREDIENTS: PILOCARPINE HYDROCHLORIDE 4 mg/1 mL
INACTIVE INGREDIENTS: HYPROMELLOSE 2910 (4000 MPA.S); SODIUM CHLORIDE; HYALURONATE SODIUM; EDETATE DISODIUM; SODIUM HYDROXIDE; HYDROCHLORIC ACID; WATER

HIGHLIGHTS OF PRESCRIBING INFORMATION

QLOSI
These highlights do not include all the information needed to use see full prescribing information for Initial U.S. Approval

1 INDICATIONS AND USAGE

QLOSI is a cholinergic agonist indicated for the treatment of presbyopia in adults. (1)

2 DOSAGE AND ADMINISTRATION

Instill one drop of QLOSI in each eye. This can be repeated a second time after 2 to 3 hours for an effect up to 8 hours. QLOSI can be administered on a daily basis, or as needed, up to twice each day. (2)

3 DOSAGE FORMS AND STRENGTHS

Ophthalmic solution: pilocarpine hydrochloride 0.4% (4 mg/mL) in a single-patient-use vial. (3)

4 CONTRAINDICATIONS

Hypersensitivity (4)

5 WARNINGS AND PRECAUTIONS

Blurred Vision: Advise patients to not drive or operate machinery if vision is not clear (e.g., blurred vision). Exercise caution in night driving and other hazardous occupations in poor illumination. (5.1)

Risk of Retinal Detachment: Rare cases of retinal detachment have been reported with miotics. Examination of the retina is advised in all patients prior to initiation of therapy. Advise patients to seek immediate medical care with sudden onset of flashes of lights, floaters, or vision loss. (5.2)

Iritis: Caution is advised in patients with iritis. (5.3)

6 ADVERSE REACTIONS

Most common adverse reactions (5% to 8%) are instillation site pain and headaches. (6.1)

To report SUSPECTED ADVERSE REACTIONS, contact Orasis Pharmaceuticals Inc. at 1-866-ORASIS1 or FDA at 1-800-FDA-1088 or www.fda.gov/medwatch.

FULL PRESCRIBING INFORMATION

1 INDICATIONS AND USAGE

QLOSI is indicated for the treatment of presbyopia in adults.

2 DOSAGE AND ADMINISTRATION

Instill one drop of QLOSI in each eye. This can be repeated a second time after 2 to 3 hours for an effect up to 8 hours. QLOSI can be administered on a daily basis, or as needed, up to twice each day.

If more than one topical ophthalmic medication is being used, the medicines must be administered at least 5 minutes apart.

Discard single-patient-use vial after use.

3 DOSAGE FORMS AND STRENGTHS

QLOSI is a clear, colorless to slightly yellowish ophthalmic solution containing pilocarpine hydrochloride 0.4% (4 mg /mL) in a single-patient-use vial.

4 CONTRAINDICATIONS

QLOSI is contraindicated in patients with known hypersensitivity to the active ingredient or to any of the excipients.

5 WARNINGS AND PRECAUTIONS

5.1 Blurred Vision

Miotics, including QLOSI, may cause accommodative spasm. Advise patients to not drive or operate machinery if vision is not clear (e.g., blurred vision).

In addition, patients may experience temporary dim or dark vision with miotics, including QLOSI. Advise patients to exercise caution in night driving and other hazardous activities in poor illumination.

5.2 Risk of Retinal Detachment

Rare cases of retinal detachment have been reported with miotics when used in susceptible individuals and those with pre-existing retinal disease. Examination of the retina is advised in all patients prior to the initiation of therapy. Advise patients to seek immediate medical care with sudden onset of flashes of lights, floaters, or vision loss.

5.3 Iritis

QLOSI is not recommended to be used when iritis is present because adhesions (synechiae) may form between the iris and the lens.

5.4 Contact Lens Wear

Contact lens wearers should be advised to remove their lenses prior to the instillation of QLOSI and to wait 10 minutes after dosing before reinserting their contact lenses.

5.5 Potential for Eye Injury or Contamination

To prevent eye injury or contamination, avoid touching the tip of the single-patient-use vial to the eye or to any other surface.

6 ADVERSE REACTIONS

6.1 Clinical Trials Experience

Because clinical trials are conducted under widely varying conditions, adverse reaction rates observed in the clinical trials of a drug cannot be directly compared to rates in the clinical trials of another drug and may not reflect the rates observed in practice.

QLOSI was evaluated in 309 patients with presbyopia in two randomized, double-masked, vehicle-controlled studies (NEAR-1 and NEAR-2) of 15 days duration. The most commonly reported treatment-related adverse events in 5-8% of patients were instillation site pain, and headache. Ocular adverse reaction reported in 2-5% of patients was blurred vision. The majority of the adverse events were mild, transient and self-resolving.

8 USE IN SPECIFIC POPULATIONS

8.1 Pregnancy

Risk Summary

There are no adequate and well-controlled studies of QLOSI administration in pregnant women to inform a drug associated risk. Oral administration of pilocarpine to pregnant rats throughout organogenesis and lactation did not produce adverse effects at clinically relevant doses.

Data

Animal Data

In embryofetal development studies, oral administration of pilocarpine to pregnant rats throughout organogenesis produced maternal toxicity, skeletal anomalies and reduction in fetal body weight at 90 mg/kg/day (approximately 1200-fold higher than the maximum recommended human ophthalmic dose [MRHOD] of 0.012mg/kg/day, on a mg/m^2basis).

In peri-/postnatal study in rats, oral administration of pilocarpine during late gestation through lactation increased stillbirths at a dose of 36 mg/kg/day (approximately 475-fold higher than the MRHOD of 0.012mg/kg/day, on a mg/m^2basis). Decreased neonatal survival and reduced mean body weight of pups were observed at ≥18mg/kg/day (approximately 240-fold higher than the MRHOD of 0.012mg/kg/day, on a mg/m^2basis).

8.2 Lactation

Risk Summary

There are no data on the presence of pilocarpine in human milk, the effects on breastfed infants, or the effects on milk production to inform the risk of QLOSI to an infant during lactation. Pilocarpine and/or its metabolites are excreted in the milk of lactating rats following single oral administration. Systemic levels of pilocarpine following topical ocular administration are low [see Clinical Pharmacology (12.3)], and it is not known whether measurable levels of pilocarpine would be present in maternal milk following ocular administration of QLOSI.

The developmental and health benefits of breastfeeding should be considered along with the mother's clinical need for QLOSI and any potential adverse effects on the breastfed child from QLOSI.

Data

Animal Data

Following a single oral administration of^14C-pilocarpine to lactating rats, the radioactivity concentrations in milk were similar to those in plasma. Peak concentrations were observed at 0.5 h, with both milk and plasma levels declining at similar rates, but still detectable at 24 h.

8.4 Pediatric Use

Presbyopia is an age-related condition which does not appear in the pediatric population.

8.5 Geriatric Use

Clinical studies of QLOSI did not include subjects aged 65 and over to determine whether they respond differently from younger subjects. Other reported clinical experience with ophthalmic pilocarpine solutions have not identified overall differences in safety between elderly and younger patients. Safety and effectiveness have not been established in patients over the age of 65.

10 OVERDOSAGE

Systemic toxicity following topical ocular administration of pilocarpine is rare, but occasionally patients who are sensitive may develop sweating and gastrointestinal overactivity.

Accidental ingestion can produce sweating, salivation, nausea, tremors and slowing of the pulse and a decrease in blood pressure.

In moderate overdosage, spontaneous recovery is to be expected and is aided by intravenous fluids to compensate for dehydration. For patients demonstrating severe poisoning, atropine, the pharmacologic antagonist to pilocarpine, should be used.

11 DESCRIPTION

QLOSI (pilocarpine hydrochloride ophthalmic solution) 0.4% is a sterile, clear, colorless to slightly yellowish and slightly viscous ophthalmic solution for topical ophthalmic use which has a pH between 5.1-6.1.

The structural formula of pilocarpine hydrochloride is:

The chemical name for pilocarpine hydrochloride is: 2(3 H)-Furanone, 3-ethyldihydro-4-[(1-methyl-1 H-imidazol-5-yl)- methyl]-monohydrochloride, (3 S-cis). Its molecular weight is 244.72 g/mol and its molecular formula is C11H16N2O2∙ HCl.

Each mL contains 0.4% (4 mg) of pilocarpine hydrochloride as the active ingredient, equivalent to 0.3% (3.4 mg) of pilocarpine free-base. The inactive ingredients in QLOSI are: hypromellose, sodium chloride, sodium hyaluronate, edetate disodium dihydrate, water for injection, and may also include sodium hydroxide and/or hydrochloric acid for pH adjustment. QLOSI does not contain an anti-microbial preservative.

12 CLINICAL PHARMACOLOGY

12.1 Mechanism of Action

Pilocarpine hydrochloride is a cholinergic muscarinic agonist which activates muscarinic receptors located at smooth muscles such as the iris sphincter muscle and ciliary muscle. QLOSI contracts the iris sphincter muscle, constricting the pupil to enhance the depth of focus and improve near visual acuity while maintaining some pupillary response to light.

12.3 Pharmacokinetics

Systemic absorption of pilocarpine was evaluated in 12 healthy subjects following QLOSI administration (2 doses daily in each eye, 2 hours apart, for 8 days). The overall median Tmaxin plasma after Day 8 dosing was 2.20 hr and the mean (SD) overall plasma Cmaxand AUC0-tafter Day 8 dosing were 897.2 (287.2) pg/mL and 2699 (741.4) hr*pg/mL, respectively. The mean T1/2after Day 8 dosing was 3.96 hr.

13 NONCLINICAL TOXICOLOGY

13.1 Carcinogenesis, Mutagenesis, Impairment of Fertility

Carcinogenesis

Lifetime oral carcinogenicity studies were conducted in CD-1 mice and Sprague-Dawley rats. Pilocarpine did not induce tumors in mice at any dosage level studies (up to 30 mg/kg/day; approximately 200-fold higher than the MRHOD of 0.012mg/kg/day, on a mg/m^2basis). In rats, an oral dose of 18 mg/kg/day (approximately 240-fold higher than the MRHOD), resulted in a statistically significant increase in the incidence of benign pheochromocytomas in both male and female rats, and a statistically significant increase in the incidence of hepatocellular adenomas in female rats.

Mutagenesis

Pilocarpine did not show any potential to cause genetic toxicity in a series of studies that included: 1) bacterial assays (Salmonella and E. coli) for reverse gene mutations; 2) an in vitro chromosome aberration assay in a Chinese hamster ovary cell line; 3) an in vivo chromosome aberration assay (micronucleus test) in mice; and 4) a primary DNA damage assay (unscheduled DNA synthesis) in rat hepatocyte primary cultures.

Impairment of Fertility

Pilocarpine oral administration to male and female rats at a dosage of 18 mg/kg/day (approximately 240-fold higher than the MRHOD of 0.012mg/kg/day, on a mg/m^2basis) resulted in impaired reproductive function, including reduced fertility, decreased sperm motility, and morphological evidence of abnormal sperm. It is unclear whether the reduction in fertility was due to effects on males, females, or both. In dogs, exposure to pilocarpine at a dosage of 3mg/kg/day for 6 months resulted in evidence of impaired spermatogenesis (approximately 135-fold higher than the MHROD of 0.012mg/kg/day, on a mg/m^2basis).

14 CLINICAL STUDIES

The efficacy of QLOSI for the treatment of presbyopia was demonstrated in two Phase 3, randomized, double-masked, vehicle-controlled studies, namely NEAR-1 (NCT04599933) and NEAR-2 (NCT04599972). A total of 613 participants aged 45 to 64 years old with presbyopia were randomized (309 to QLOSI group) in these two studies. Participants were instructed to instill one drop of QLOSI or vehicle, in each eye, once in the morning and to repeat the instillation 2 to 3 hours later. Participants were treated for two weeks. Ophthalmic assessments were conducted on Day 1, 8 and 15 of the study at various timepoints.

Responders demonstrated improvement by achieving a gain from baseline of 3 lines or more in near BDCVA at 40 centimeters without a loss of 1 line or more (≥ 5 letters) in BDCVA at 4 meters. Overall, the percentages of responders were consistently higher in the QLOSI group than in the Vehicle group at each assessment day.

Table 1: Primary and key secondary results from NEAR-1 and NEAR-2 studies: Percentage of Responders - Day 8
 | NEAR-1 |  |  | NEAR-2
Assessment timing | QLOSI N=155 | Vehicle N=154 | p-value | QLOSI N=154 | Vehicle N=150 | p-value
1 hour post Dose 1 | 39% | 17% | <0.01 | 42% | 21% | <0.01
2 hours post Dose 1 | 39% | 17% | <0.01 | 40% | 21% | <0.01
1 hour post Dose 2 | 48% | 16% | <0.01 | 52% | 17% | <0.01
2 hours post Dose 2 | 39% | 15% | <0.01 | 46% | 19% | <0.01
Abbreviations: N: number of participants in this study arm

Figure 1 presents the percentage of responders for each time point at Day 15. (Standard analysis of pooled data NEAR-1 and NEAR-2)

Abbreviations: HRS: hours; min: minutes

This figure demonstrates the onset of the QLOSI effect on presbyopia, from 20 minutes post dose 1, and lasting up to 8 hours (i.e., 5 hours from the second dose).

17 PATIENT COUNSELING INFORMATION

Night Driving

QLOSI may cause temporary dim or dark vision. Advise patients to exercise caution with night driving and when hazardous activities are undertaken in poor illumination.

Blurred Vision

Temporary problems when changing focus between near objects and distant objects may occur. Advise patients to not drive or use machinery if vision is not clear.

When to Seek Physician Advice

Advise patients to seek immediate medical care with sudden onset of flashing lights, floaters, or vision loss [see Warnings and Precautions (5.2)].

Contact Lens Wear

Advise patients to remove contact lenses prior to the instillation of QLOSI. Wait 10 minutes after dosing before reinserting contact lenses.

Potential for Eye Injury or Contamination

Advise patients to avoid touching the tip of the single-patient-use vial to the eye or to any other surface, in order to prevent eye injury or contamination.

Concomitant Topical Ocular Therapy

Advise patients if more than one topical ophthalmic medication is being used, the medicines must be administered at least 5 minutes apart.

Storage Information

Store refrigerated at 36°F to 46°F (2°C to 8°C). Once a pouch is open, the single-patient-use vials may be stored at room temperature [up to 77°F (25°C)] and used within 30 days.

Store unused product away from light. Discard opened vials after use.

16 HOW SUPPLIED/ STORAGE AND HANDLING

16.1 How Supplied

QLOSI is supplied as a sterile, clear, colorless to slightly yellowish and slightly viscous ophthalmic solution in configurations of 5 single-patient-use vials of 0.4 mL fill. Each single-patient-use vial is comprised of transparent low-density polyethylene (LDPE).

5 single-patient-use vials are packaged in a foil pouch.

QLOSI is supplied in:

NDC 83661-018-10: carton box of 10 single-patient-use vials (2 pouches containing 5 vials)

NDC 83661-018-20: carton box of 20 single-patient-use vials (4 pouches containing 5 vials)

NDC 83661-018-30: carton box of 30 single-patient-use vials (6 pouches containing 5 vials)

NDC 83661-018-60: carton box of 60 single-patient-use vials (12 pouches containing 5 vials)

16.2 Storage

Store refrigerated at 36°F to 46°F (2°C to 8°C). Once a pouch is open, the single-patient-use vials may be stored at room temperature [up to 77°F (25°C)] and used within 30 days.

Store unused product away from light. Discard opened vials after use.

Manufactured for:

Orasis Pharmaceuticals, Inc.

Ponte Vedra, FL 32081

PRINCIPAL DISPLAY PANEL - 0.4 mL Vial Box

Qlosi™
(pilocarpine HCl
ophthalmic
solution) 0.4%

Sterile / Rx only

For topical application in the eye

6 pouches containing 5 single-
patient-use vials (0.4 mL each)

NDC 83661-018-30